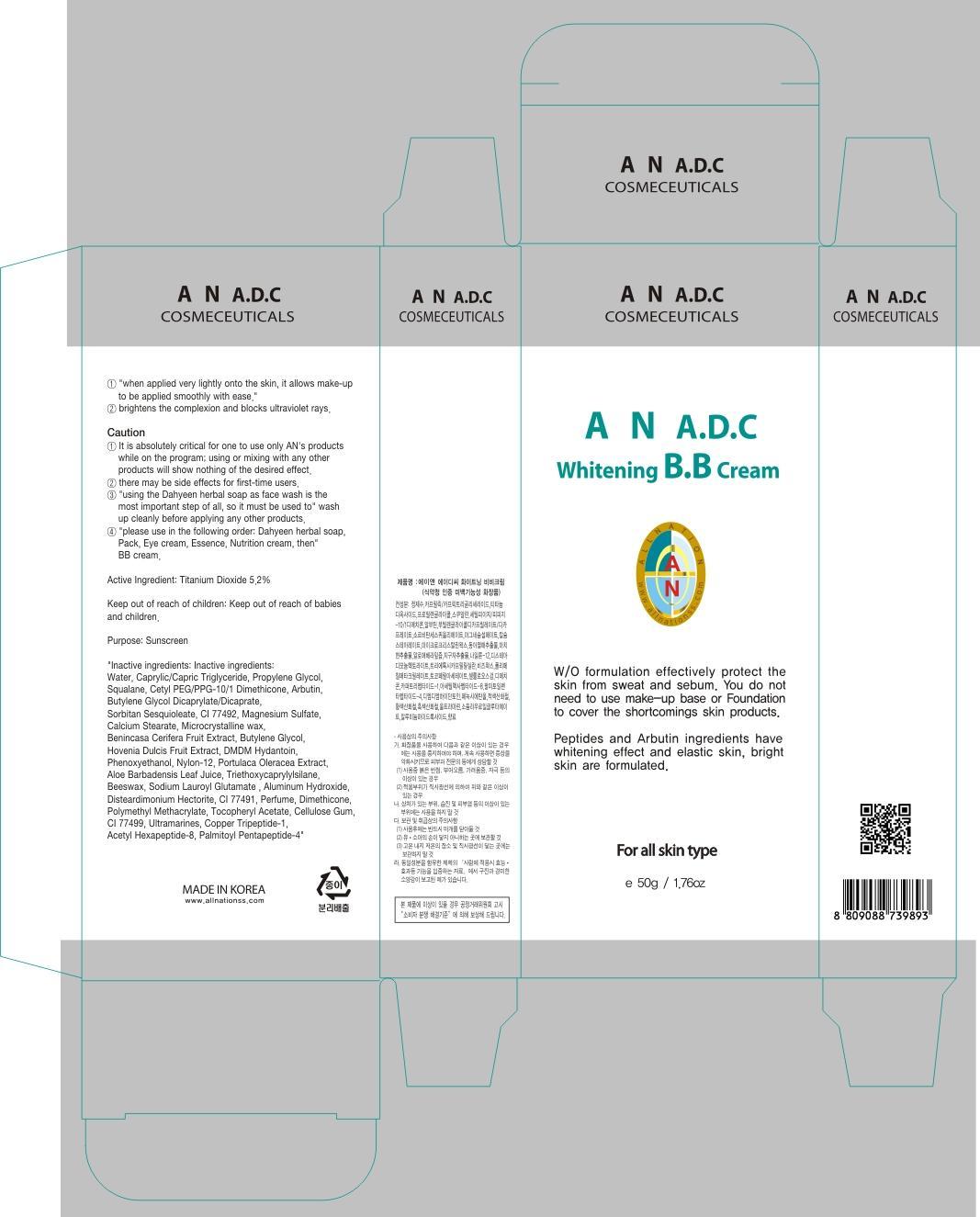 DRUG LABEL: AN ADC WHITENING BB
NDC: 69153-060 | Form: CREAM
Manufacturer: AN Co Ltd.
Category: otc | Type: HUMAN OTC DRUG LABEL
Date: 20140929

ACTIVE INGREDIENTS: Titanium Dioxide 2.6 g/50 g
INACTIVE INGREDIENTS: Water; Propylene Glycol

ACTIVE INGREDIENT

Active Ingredient: Titanium Dioxide 5.2%

INACTIVE INGREDIENT

Inactive ingredients: Water, Caprylic/Capric Triglyceride, Propylene Glycol, Squalane, Cetyl PEG/PPG-10/1 Dimethicone, Arbutin, Butylene Glycol Dicaprylate/Dicaprate, Sorbitan Sesquioleate, CI 77492, Magnesium Sulfate, Calcium Stearate, Microcrystalline wax, Benincasa Cerifera Fruit Extract, Butylene Glycol, Hovenia Dulcis Fruit Extract, DMDM Hydantoin, Phenoxyethanol, Nylon-12, Portulaca Oleracea Extract, Aloe Barbadensis Leaf Juice, Triethoxycaprylylsilane, Beeswax, Sodium Lauroyl Glutamate , Aluminum Hydroxide, Disteardimonium Hectorite, CI 77491, Perfume, Dimethicone, Polymethyl Methacrylate, Tocopheryl Acetate, Cellulose Gum, CI 77499, Ultramarines, Copper Tripeptide-1, Acetyl Hexapeptide-8, Palmitoyl Pentapeptide-4

PURPOSE

Purpose: Sunscreen

Caution

1. It is absolutely critical for one to use only AN's products while on the program; using or mixing with any other products will show nothing of the desired effect.
2. There may be side effects for first-time users.
3. Using the Dahyeen herbal soap as face wash is the most important step of all, so it must be used to wash up cleanly before applying any other products.
4. Please use in the following order: Dahyeen herbal soap, Pack, Eye cream, Essence, Nutrition cream, then BB cream.

Keep out of reach of children: Keep out of reach of babies and children.

INDICATIONS & USAGE

1. When applied very lightly onto the skin, it allows make-up to be applied smoothly with ease.
2. Brightens the complexion and blocks ultraviolet rays.

DOSAGE & ADMINISTRATION

1. When applied very lightly onto the skin, it allows make-up to be applied smoothly with ease.
2. Brightens the complexion and blocks ultraviolet rays.